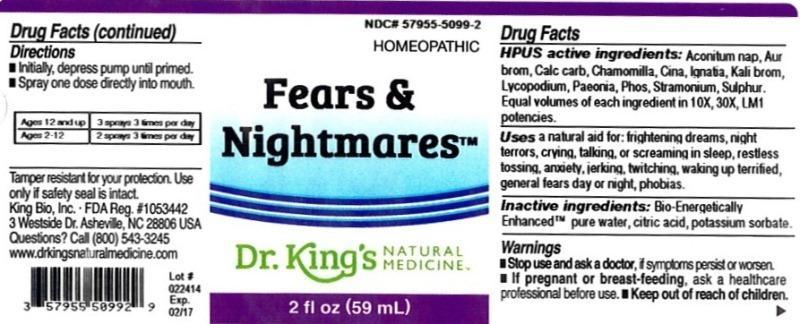 DRUG LABEL: Fears and Nightmares
NDC: 57955-5099 | Form: LIQUID
Manufacturer: King Bio Inc.
Category: homeopathic | Type: HUMAN OTC DRUG LABEL
Date: 20140401

ACTIVE INGREDIENTS: ACONITUM NAPELLUS 10 [hp_X]/59 mL; GOLD TRIBROMIDE 10 [hp_X]/59 mL; OYSTER SHELL CALCIUM CARBONATE, CRUDE 10 [hp_X]/59 mL; MATRICARIA RECUTITA 10 [hp_X]/59 mL; ARTEMISIA CINA PRE-FLOWERING TOP 10 [hp_X]/59 mL; STRYCHNOS IGNATII SEED 10 [hp_X]/59 mL; POTASSIUM BROMIDE 10 [hp_X]/59 mL; LYCOPODIUM CLAVATUM SPORE 10 [hp_X]/59 mL; PAEONIA OFFICINALIS ROOT 10 [hp_X]/59 mL; PHOSPHORUS 10 [hp_X]/59 mL; DATURA STRAMONIUM 10 [hp_X]/59 mL; SULFUR 10 [hp_X]/59 mL
INACTIVE INGREDIENTS: WATER; CITRIC ACID MONOHYDRATE; POTASSIUM SORBATE

Fears and Nightmares

ACTIVE INGREDIENT

HPUS active ingredients: Aconitum napellus, Aurum bromatum, Calcarea carbonica, Chamomilla, Cina, Ignatia amara, Kali bromatum, Lycopodium clavatum, Paeonia officinalis, Phosphorus, Stramonium, Sulphur. Equal volumes of each ingredient in 10X, 30X, LM1 potencies.

PURPOSE

Uses a natural aid for: frightening dreams, night terrors, crying, talking or screaming in sleep, restless tossing, anxiety, jerking, twitching, waking up terrified, general fears day or night, phobias.

Inactive Ingredients:

Bio-Energetically Enhanced™ pure water base, Citric acid and Potassium sorbate.

Warning

- Stop use and ask a doctor. If symptoms persist or worsen.
- If pregnant or breast-feeding, ask a healthcare professional before use.

- Keep out of reach of children

Directions

- Initially, depress pump until primed.
- Spray one dose directly into mouth.
- Ages 12 and up 3 sprays 3 times per day.
- Ages 2-12 2 sprays 3 times per day.

Other Information: Tamper resistant for your protection. Use only if safety seal is intact.

INDICATIONS AND USAGE

Uses a natural aid for:

- frightening dreams
- night terrors
- crying, talking or screaming in sleep
- restless tossing
- anxiety, jerking, twitching, waking up terrified
- general fears day or night
- phobias